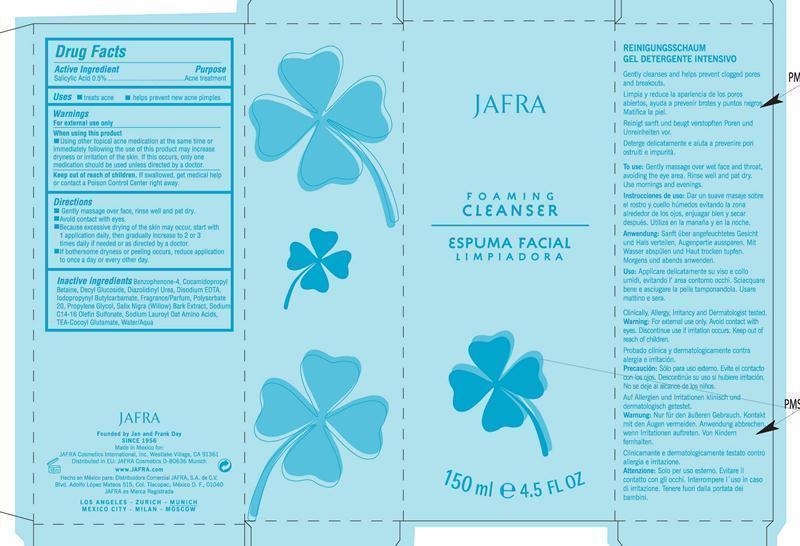 DRUG LABEL: Foaming Cleanser

NDC: 68828-096 | Form: GEL
Manufacturer: JAFRA COSMETICS INTERNATIONAL
Category: otc | Type: HUMAN OTC DRUG LABEL
Date: 20200622

ACTIVE INGREDIENTS: SALICYLIC ACID 0.5 g/100 mL
INACTIVE INGREDIENTS: SULISOBENZONE; COCAMIDOPROPYL BETAINE; DECYL GLUCOSIDE; DIAZOLIDINYL UREA; EDETATE DISODIUM; IODOPROPYNYL BUTYLCARBAMATE; POLYSORBATE 20; PROPYLENE GLYCOL; SALIX NIGRA BARK; SODIUM C14-16 OLEFIN SULFONATE; SODIUM LAUROYL OAT AMINO ACIDS; WATER

Jafra Foaming Cleanser

Active Ingredient Purpose

Salicyclic Acid 0.5% Acne Treatment

Uses

Treats acne

Prevents new acne pimples

Keep out of reach of children. If swallowed, get medical help or contact a Poison Control Center right away.

indications and usage

When using this product

Using other topical acne medication at the same time or immediately following the use of this product may increase dryness or irritation of the skin. If this occurs, only one medication should be used unless directed by a doctor.

Warnings

For external use only

Directions

-Gently massage over face, rinse well and pat dry.
-Avoid contact with eyes.
-Because excessive drying of the skin may occur, start with
1 application daily, then gradually increase to 2 or 3
times daily if needed or as directed by a doctor.
-If bothersome dryness or peeling occurs, reduce application
to once a day or every other day.

Inactive ingredients

Benzophenone-4, cocamidopropyl
Betaine, Decyl Glucoside, Diazolidinyl Urea, Disodium EDTA,
lodopropynyl Butylcarbamate, Fragrance/Parfum, Polysorbate
20, Propylene Glycol, Salix Nigra (Willow) Bark Extract, Sodium
C14-16 Olefin Sulfonate, Sodium Lauroyl Oat Amino Acids,
TEA-Cocoyl Glutamate, Water/Aqua.

PACKAGE LABEL

Jafra

Foaming Cleanser

Espuma Facial Limpiadora

150 ml 4.5 Fl Oz